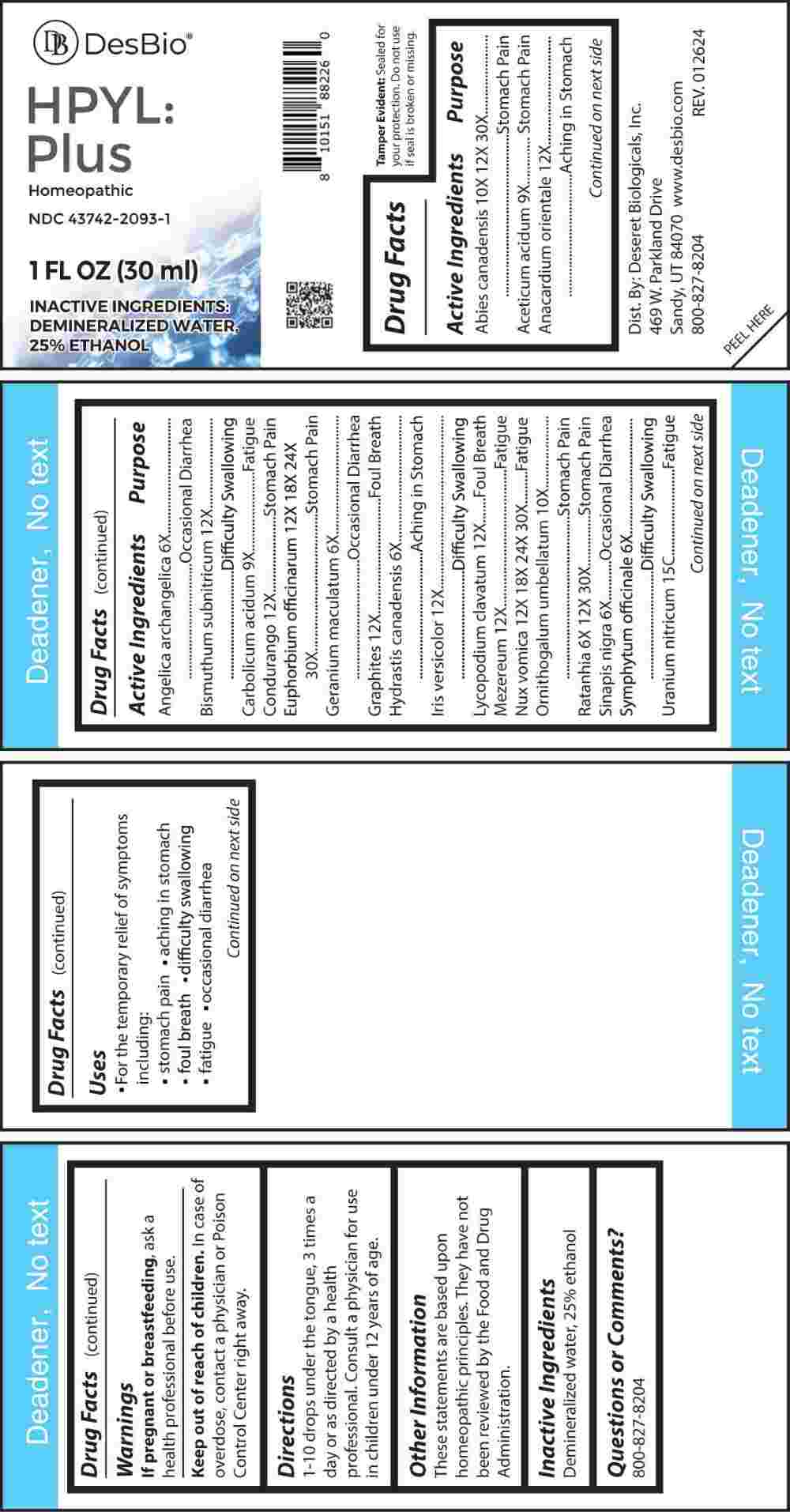 DRUG LABEL: HPYL PLUS
NDC: 43742-2093 | Form: LIQUID
Manufacturer: Deseret Biologicals, Inc.
Category: homeopathic | Type: HUMAN OTC DRUG LABEL
Date: 20240426

ACTIVE INGREDIENTS: ANGELICA ARCHANGELICA ROOT 6 [hp_X]/1 mL; GERANIUM MACULATUM ROOT 6 [hp_X]/1 mL; GOLDENSEAL 6 [hp_X]/1 mL; BLACK MUSTARD SEED 6 [hp_X]/1 mL; COMFREY ROOT 6 [hp_X]/1 mL; KRAMERIA LAPPACEA ROOT 6 [hp_X]/1 mL; ACETIC ACID 9 [hp_X]/1 mL; PHENOL 9 [hp_X]/1 mL; ORNITHOGALUM UMBELLATUM WHOLE 10 [hp_X]/1 mL; TSUGA CANADENSIS FLOWER BUD 10 [hp_X]/1 mL; TSUGA CANADENSIS BARK 10 [hp_X]/1 mL; SEMECARPUS ANACARDIUM JUICE 12 [hp_X]/1 mL; BISMUTH SUBNITRATE 12 [hp_X]/1 mL; RUEHSSIA CUNDURANGO BARK 12 [hp_X]/1 mL; GRAPHITE 12 [hp_X]/1 mL; IRIS VERSICOLOR ROOT 12 [hp_X]/1 mL; LYCOPODIUM CLAVATUM SPORE 12 [hp_X]/1 mL; DAPHNE MEZEREUM BARK 12 [hp_X]/1 mL; EUPHORBIA RESINIFERA RESIN 12 [hp_X]/1 mL; STRYCHNOS NUX-VOMICA SEED 12 [hp_X]/1 mL; URANYL NITRATE HEXAHYDRATE 15 [hp_C]/1 mL
INACTIVE INGREDIENTS: WATER; ALCOHOL

DRUG FACTS:

ACTIVE INGREDIENTS:

Abies Canadensis 10X, 12X, 30X, Aceticum Acidum 9X, Anacardium Orientale 12X, Angelica Archangelica 6X, Bismuthum Subnitricum 12X, Carbolicum Acidum 9X, Condurango 12X, Euphorbium Officinarum 12X, 18X, 24X, 30X, Geranium Maculatum 6X, Graphites 12X, Hydrastis Canadensis 6X, Iris Versicolor 12X, Lycopodium Clavatum 12X, Mezereum 12X, Nux Vomica 12X, 18X, 24X, 30X, Ornithogalum Umbellatum 10X, Ratanhia 6X, 12X, 30X, Sinapis Nigra 6X, Symphytum Officinale 6X, Uranium Nitricum 15C.

PURPOSE:

Abies Canadensis – Stomach Pain, Aceticum Acidum – Stomach Pain, Anacardium Orientale -
Aching in Stomach, Angelica Archangelica – Occasional Diarrhea, Bismuthum Subnitricum – Difficulty Swallowing, Carbolicum Acidum - Fatigue, Condurango – Stomach Pain, Euphorbium Officinarum – Stomach Pain, Geranium Maculatum – Occasional Diarrhea, Graphites – Foul Breath, Hydrastis Canadensis – Aching in Stomach, Iris Versicolor – Difficulty Swallowing, Lycopodium Clavatum – Foul Breath, Mezereum - Fatigue, Nux Vomica - Fatigue, Ornithogalum Umbellatum – Stomach Pain, Ratanhia – Stomach Pain, Sinapis Nigra – Occasional Diarrhea, Symphytum Officinale – Difficulty Swallowing, Uranium Nitricum - Fatigue

USES:

• For the temporary relief of symptoms including:

• stomach pain • aching in stomach • foul breath

• difficulty swallowing • fatigue • occasional diarrhea

These statements are based upon homeopathic principles. They have not been reviewed by the Food and Drug Administration.

WARNINGS:

If pregnant or breast-feeding, ask a health professional before use.

Keep out of reach of children. In case of overdose, contact a physician or a Poison Control Center right away.

Tamper Evident: Sealed for your protection. Do not use if seal is broken or missing.

KEEP OUT OF REACH OF CHILDREN:

In case of overdose, contact a physician or Poison Control Center right away.

DIRECTIONS:

1-10 drops under the tongue, 3 times a day or as directed by a health professional. Consult a physician for use in children under 12 years of age.

INACTIVE INGREDIENTS:

Demineralized water, 25% ethanol

QUESTIONS:

Dist. By: Deseret Biologicals, Inc.
469 W. Parkland Drive
Sandy, UT 84070

www.desbio.com

800-827-8204

PACKAGE LABEL DISPLAY:

Des Bio

HPYL:Plus

Homeopathic

NDC 43742-2093-1

1 FL OZ (30 ml)